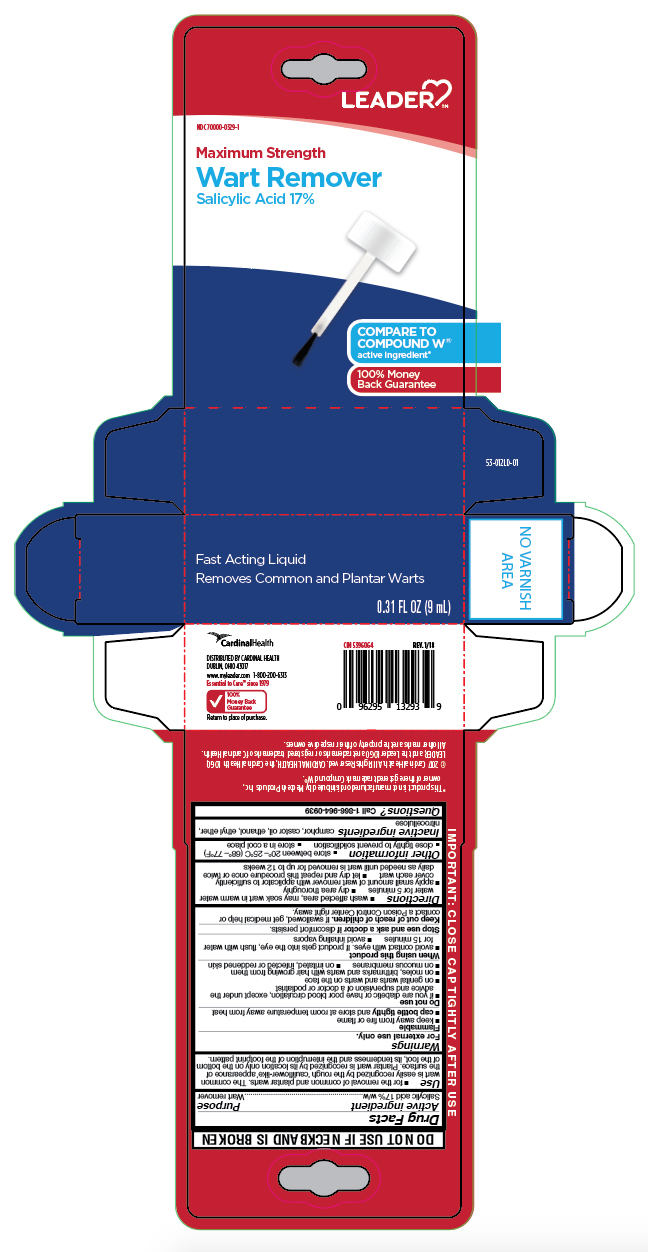 DRUG LABEL: Salicylic Acid
NDC: 70000-0329 | Form: LIQUID
Manufacturer: LEADER/ Cardinal Health 110, Inc.
Category: otc | Type: HUMAN OTC DRUG LABEL
Date: 20251231

ACTIVE INGREDIENTS: SALICYLIC ACID 17 g/100 mL
INACTIVE INGREDIENTS: ALCOHOL; PYROXYLIN; CAMPHOR (NATURAL); CASTOR OIL; ETHYL ETHER

Leader Liquid Wart Remover

Active ingredient

Salicylic acid 17%w/w

Purpose

Wart remover

Use

- for the removal of common and plantar warts. The common wart is easily recognized by the rough 'cauliflower-like' appearance of the surface. Plantar wart is recognized by its location only on the bottom of the foot, its tenderness and the interruption of the footprint pattern.

Warnings

For external use only.

Flammable

- keep away from fire or flame
- cap bottle tightly and store at room temperature away heat

Do not use

- if you are a diabetic or have poor blood circulation, except under the supervision of a doctor or podiatrist
- on genital warts and warts on the face
- on moles, birthmarks and warts with hair growing from them
- on mucous membranes
- on irritated, infected or reddened skin

When using this product

- avoid contact with eyes. If product gets into the eye, flush with water for 15 minutes
- avoid inhaling vapors

Stop use and ask a doctor if

discomforts persists.

Keep out of reach of children.

If swallowed, get medical help or contact a Poison Control Center right away.

Directions

- wash affected area, may soak wart in warm water for 5 minutes
- dry area thoroughly
- apply small amount of wart remover with applicator to sufficiently cover each wart
- let dry and repeat this procedure once or twice daily as needed until wart is removed for up to 12 weeks

Other information

- store between 20°-25°C (68°- 77°F)
- close tightly to prevent solidification
- store in a cool place

Inactive ingredients

camphor, castor oil, ethanol, ethyl ether, nitrocellulose

Questions?

Call 1-800-200-6313

Principal Display Panel

LEADER

Maximum Strength

Wart Remover

Salicylic Acid 17%

Fast acting Liquid

Removes Common and Plantar Warts

NET 0.31 FL OZ (9 mL)